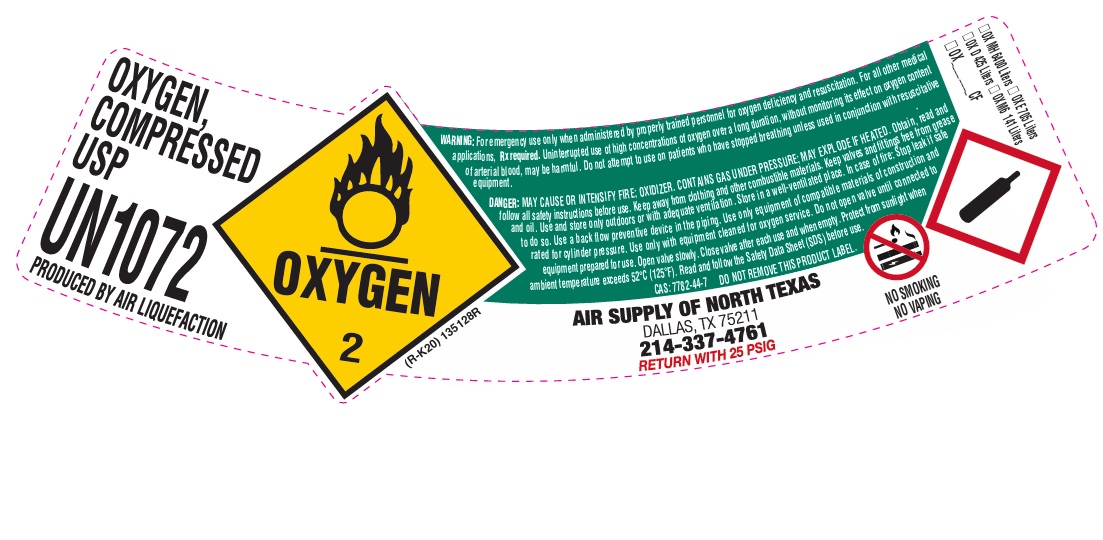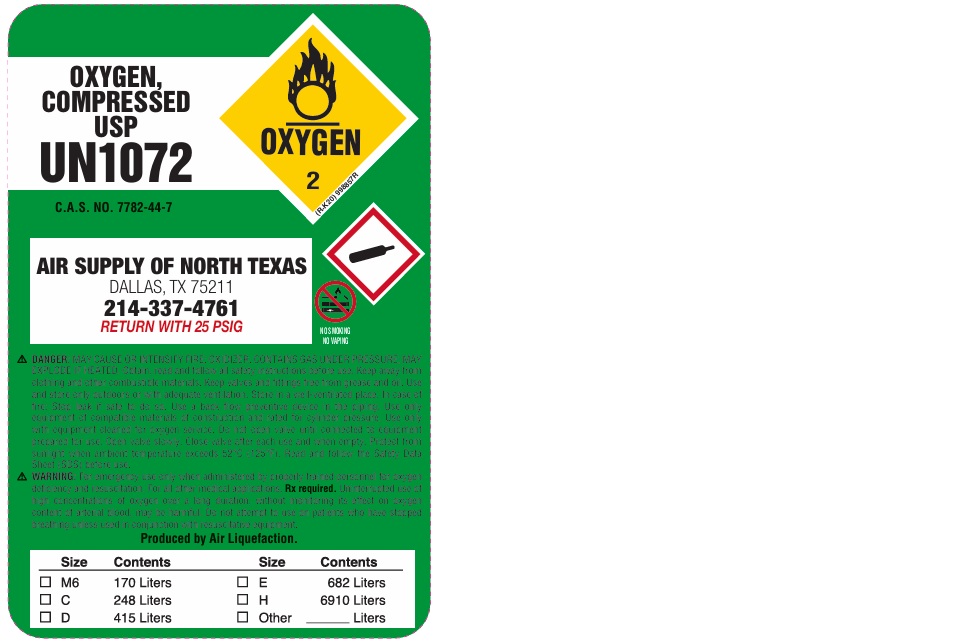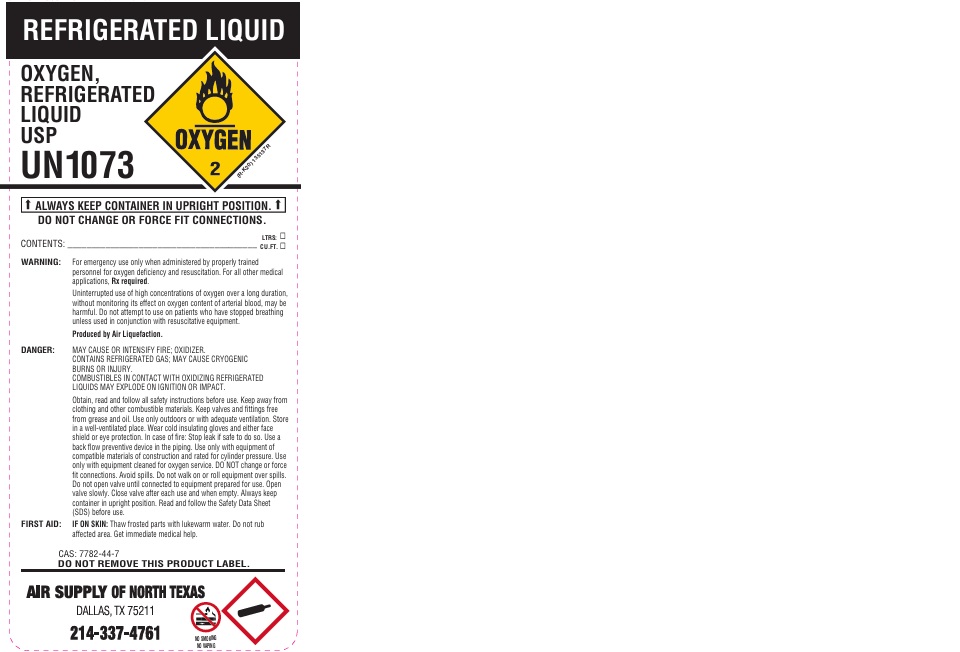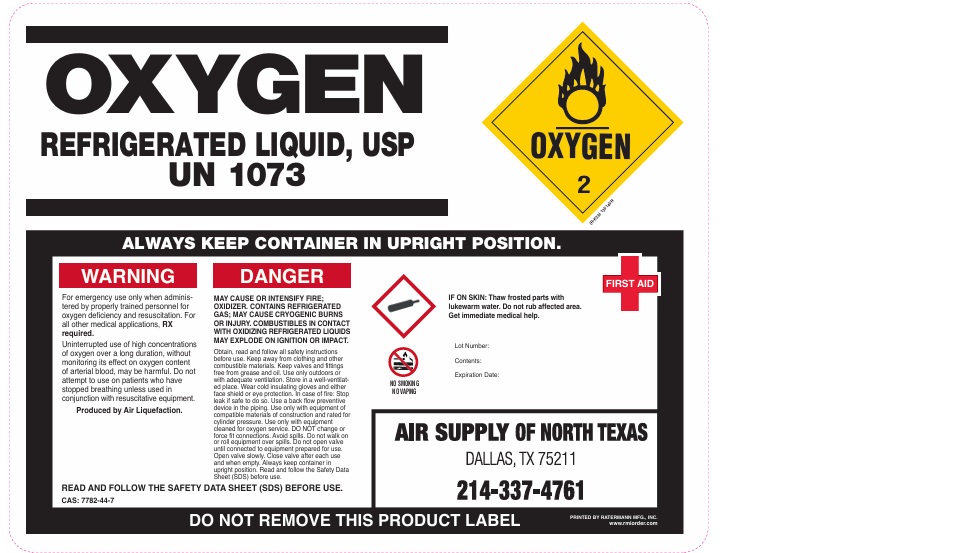 DRUG LABEL: Oxygen
NDC: 63978-011 | Form: Gas
Manufacturer: QUALITY AIR PRODUCTS INC
Category: animal | Type: PRESCRIPTION ANIMAL DRUG LABEL
Date: 20251216

ACTIVE INGREDIENTS: OXYGEN 990 mL/1 L

Oxygen

PACKAGE LABEL

OXYGEN, COMPRESSED USP
UN1072
PRODUCED BY AIR LIQUEFACTION
WARNING: For emergency use only when administered by properly trained personnel for oxygen deficiency and resuscitation. For all other medical applications, Rx required. Uninterrupted use on high concentrations of oxygen over a long duration, without monitoring its effect on oxygen content of arterial blood, may be harmful. Do not attempt to use on patients who have stopped breathing unless used in conjunction with resuscitative equipment.
DANGER: MAY CAUSE OR INTENSIFY FIRE; OXIDIZER. CONTAINS GAS UNDER PRESSURE; MAY EXPLODE IF HEATED. Obtain, read and follow all safety instructions before use. Keep away from clothing and other combustible materials. Keep valves and fittings free from grease and oil. Use and store only outdoors or with adequate ventilation. Store in a well-ventilated place. In case of fire: Stop leak if safe to do so. Use a back flow preventive device in the piping. Use only equipment of compatible materials of construction and rated for cylinder pressure. Use only with equipment cleaned for oxygen service. Do not open valve until connected to equipment prepared for use. Open valve slowly. Close valve after each use and when empty. Protect from sunlight when ambient temperature exceeds 52 C (125 F). Read and follow the Safety Data Sheet (SDS) before use.
CAS: 7782-44-7 DO NOT REMOVE THIS PRODUCT LABEL.
AIR SUPPLY OF NORTH TEXAS
DALLAS, TX 75211
214-337-4761
RETURN WITH 25 PSIG
NO SMOKING
NO VAPING
OX MH 6400 Liters OX E 705 Liters
OX D 425 Liters OX M6 141 Liters
OX CF

PACKAGE LABEL

OXYGEN, COMPRESSED USP
UN1072
C.A.S. NO. 7782-44-7
AIR SUPPLY OF NORTH TEXAS
DALLAS, TX 75211
214-337-4761
RETURN WITH 25 PSIG
NO SMOKING
NO VAPING
DANGER: MAY CAUSE OR INTENSIFY FIRE; OXIDIZER. CONTAINS GAS UNDER PRESSURE; MAY EXPLODE IF HEATED. Obtain, read and follow all safety instructions before use. Keep away from clothing and other combustible materials. Keep valves and fittings free from grease and oil. Use and store only outdoors or with adequate ventilation. Store in a well-ventilated place. In case of fire: Stop leak if safe to do so. Use a back flow preventive device in the piping. Use only equipment of compatible materials of construction and rated for cylinder pressure. Use only with equipment cleaned for oxygen service. Do not open valve until connected to equipment prepared for use. Open valve slowly. Close valve after each use and when empty. Protect from sunlight when ambient temperature exceeds 52 C (125 F). Read and follow the Safety Data Sheet (SDS) before use.
WARNING: For emergency use only when administered by properly trained personnel for oxygen deficiency and resuscitation. For all other medical applications, Rx required. Uninterrupted use of high concentrations of oxygen over a long duration, without monitoring its effect on oxygen content of arterial blood, may be harmful. Do not attempt to use on patients who have stopped breathing unless used in conjunction with resuscitative equipment.
Produced by Air Liquefaction.
Size Contents Size Contents
M6 170 Liters E 682 Liters
C 248 Liters H 6910 Liters
D 415 Liters Other Liters

PACKAGE LABEL

REFRIGERATED LIQUID
OXYGEN, REFRIGERATED LIQUID USP
UN1073
ALWAYS KEEP CONTAINER IN UPRIGHT POSITION.
DO NOT CHANGE OR FORCE FIT CONNECTIONS
CONTENTS: LTRS: CU.FT.
WARNING: For emergency use only when administered by properly trained personnel for oxygen deficiency and resuscitation. For all other medical applications, Rx required.
Uninterrupted use of high concentrations of oxygen over a long duration, without monitoring its effect on oxygen content of arterial blood, may be harmful. Do not attempt to use on patients who have stopped breathing unless used in conjunction with resuscitative equipment.
Produced by Air Liquefaction.
DANGER: MAY CAUSE OR INTENSIFY FIRE; OXIDIZER. CONTAINS REFRIGERATED GAS; MAY CAUSE CRYOGENIC BURNS OR INJURY. COMBUSTIBLES IN CONTACT WITH OXIDIZING REFRIGERATED LIQUIDS MAY EXPLODE ON IGNITION OR IMPACT.
Obtain, read and follow all safety instructions before use. Keep away from clothing and other combustible materials. Keep valves and fittings free from grease and oil. Use only outdoors or with adequate ventilation. Store in a well-ventilated place. Wear cold insulating gloves and either face shield or eye protection. In case of fire: Stop leak if safe to do so. Use a back flow preventive device in the piping. Use only with equipment of compatible materials of construction and rated for cylinder pressure. Use only with equipment cleaned for oxygen service. DO NOT change or force fit connections. Avoid spills. Do not walk on or roll equipment over spills. Do not open valve until connected to equipment prepared for use. Open valve slowly. Close valve after each use and when empty. Always keep container in upright position. Read and follow the Safety Data Sheet (SDS) before use.
FIRST AID: IF ON SKIN: Thaw frosted parts with lukewarm water. Do not rub affected area. Get immediate medical help.
CAS: 7782-44-7
DO NOT REMOVE THIS PRODUCT LABEL.
AIR SUPPLY OF NORTH TEXAS
DALLAS, TX 75211
214-337-4761
RETURN WITH 25 PSIG
NO SMOKING
NO VAPING

PACKAGE LABEL

OXYGEN REFRIGERATED LIQUID, USP
UN 1073
ALWAYS KEEP CONTAINER IN UPRIGHT POSITION.
WARNING
For emergency use only when administered by properly trained personnel for oxygen deficiency and resuscitation. For all other medical applications, Rx required.
Uninterrupted use of high concentrations of oxygen over a long duration, without monitoring its effect on oxygen content of arterial blood, may be harmful. Do not attempt to use on patients who have stopped breathing unless used in conjunction with resuscitative equipment.
Produced by Air Liquefaction.
DANGER
MAY CAUSE OR INTENSIFY FIRE; OXIDIZER. CONTAINS REFRIGERATED GAS; MAY CAUSE CRYOGENIC BURNS OR INJURY. COMBUSTIBLES IN CONTACT WITH OXIDIZING REFRIGERATED LIQUIDS MAY EXPLODE ON IGNITION OR IMPACT.
Obtain, read and follow all safety instructions before use. Keep away from clothing and other combustible materials. Keep valves and fittings free from grease and oil. Use only outdoors or with adequate ventilation. Store in a well-ventilated place. Wear cold insulating gloves and either face shield or eye protection. In case of fire: Stop leak if safe to do so. Use a back flow preventive device in the piping. Use only with equipment of compatible materials of construction and rated for cylinder pressure. Use only with equipment cleaned for oxygen service. DO NOT change or force fit connections. Avoid spills. Do not walk on or roll equipment over spills. Do not open valve until connected to equipment prepared for use. Open valve slowly. Close valve after each use and when empty. Always keep container in upright position. Read and follow the Safety Data Sheet (SDS) before use.
READ AND FOLLOW THE SAFETY DATA SHEET (SDS) BEFORE USE.
CAS: 7782-44-7
NO SMOKING
NO VAPING
FIRST AID
IF ON SKIN: Thaw frosted parts with lukewarm water. Do not rub affected area. Get immediate medical help.
Lot Number:
Contents:
Expiration Date:
AIR SUPPLY OF NORTH TEXAS
DALLAS, TX 75211
214-337-4761
DO NOT REMOVE THIS PRODUCT LABEL